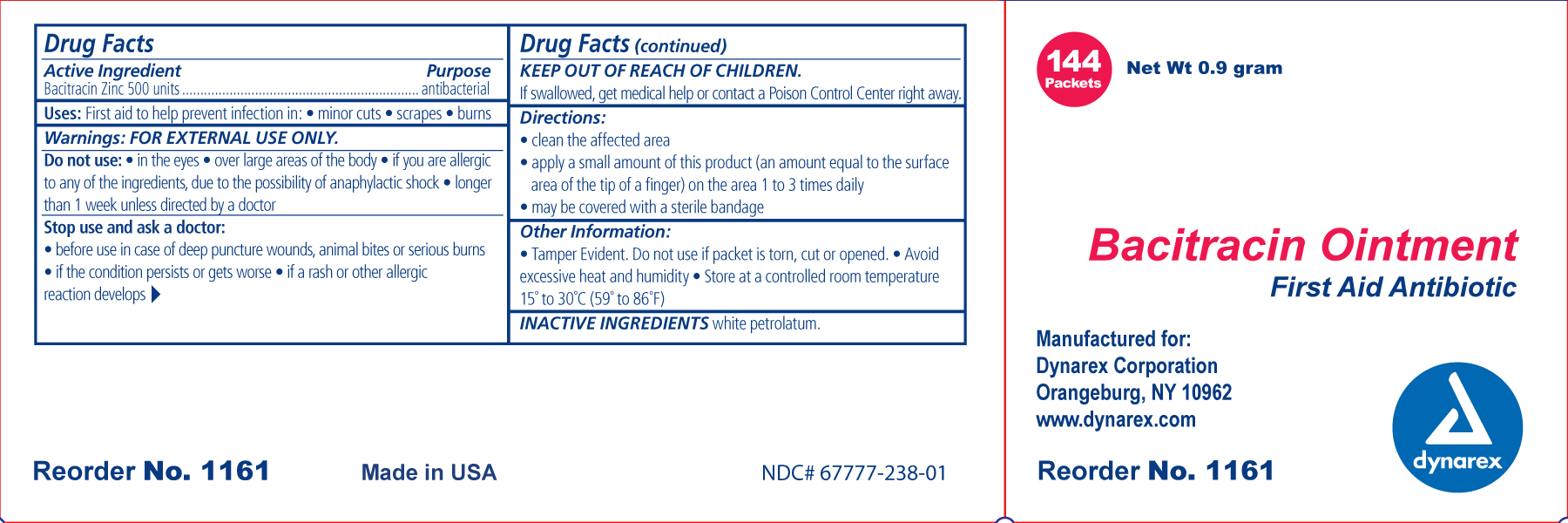 DRUG LABEL: Bacitracin Zinc
NDC: 67777-238 | Form: OINTMENT
Manufacturer: Dynarex Corporation
Category: otc | Type: HUMAN OTC DRUG LABEL
Date: 20110323

ACTIVE INGREDIENTS: BACITRACIN ZINC 500 [iU]/1 g
INACTIVE INGREDIENTS: PETROLATUM

Bacitracin

Active ingredient Purpose
Bacitracin Zinc 500 Units Antibactrerial

Uses Bacitracin:

First aid to help prevent infection in:

- Minor cuts
- scrapes
- burns

Ask a doctor before use:

- in case of deep or puncture wounds, animal bites and serious burns
- if the condition persists or gets worse
- if a rash or any other allergic reaction develops

Other information

- store at controlled room temperature 15°-30° C (59°-86° F)
- Tamper Evident. Do not use if packet is torn, cut or opened.

Inactive ingredients

White Petrolatum

Indications and Usage

- For first aid to help prevent infection in minor skin abrasions and rashes.

Directions:

- clean the affected area
- apply a small amount of this product (an amount equal to the surface area of the tip of the finger) on the area 1-3 times daily.
- may be covered with a sterile bandage

KEEP OUT OF REACH OF CHILDREN. If swallowed, get medical help or contact a Poison Control Center right away.

WARNINGS

- for external use only

Do not use:

- in the eyes
- over large area of the body
- if you are allergic to any of the ingredients, due to the possibility of anaphylactic shock
- longer than 1 week unless directed by a doctor

Principal Display Panel